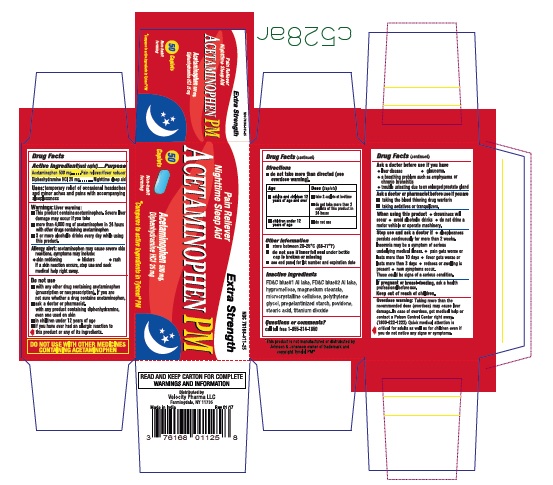 DRUG LABEL: Pain Relief PM
NDC: 76168-119 | Form: TABLET
Manufacturer: Velocity Pharma
Category: otc | Type: HUMAN OTC DRUG LABEL
Date: 20180514

ACTIVE INGREDIENTS: ACETAMINOPHEN 500 mg/1 1; DIPHENHYDRAMINE HYDROCHLORIDE 25 mg/1 1
INACTIVE INGREDIENTS: SILICON DIOXIDE; CROSCARMELLOSE SODIUM; FD&C BLUE NO. 1; FD&C BLUE NO. 2; HYPROMELLOSES; CELLULOSE, MICROCRYSTALLINE; POVIDONE; SODIUM METABISULFITE; STEARIC ACID; TITANIUM DIOXIDE; SODIUM STARCH GLYCOLATE TYPE A POTATO; TALC; POLYETHYLENE GLYCOL 1000

Acetaminophen, Diphenhydramine HCl Tablets

Active Ingredient

(in each tablet)

Acetaminophen 500mg

Diphenhydramine HCl 25mg

Purpose

pain reliever/fever reducer

Nighttime sleep aid

Uses

- temporarily relief of occasional headaches and minor aches and pains with accompanying sleeplessness

Warnings

Liver Warning: This product contains acetaminophen. Severe liver damage may occur if you take

- more than 4000 mg of acetaminophen in 24 hours
- with other drugs containing acetaminophen
- 3 or more alcoholic drinks everyday while using this product

- Overdose warning: Taking more than recommended dose (overdose) may cause liver damage. In case of overdose, get medical help or contact a Poison Control Center right away. Prompt medical attention is critical for adults as well as for children even if you do not notice any signs or symptoms.

do not use

- with any other drug containing acetaminophen (prescription or not prescription). If you are not sure whether a drug contains acetaminophen, ask a doctor or pharmacist.
- With any other product containing diphenhydramine, even one used on skin.
- In children under 12 years of age
- With other products containing diphenhydramine, even one used on skin.

ask a doctor before use if you have

- liver disease
- asthma
- a breathing problem such as emphysema or chronic bronchitis
- trouble urinating due to an enlarged prostate gland
- galucoma

ask your doctor or pharmacist before use if you are

- taking the blood thinning drug warfarin
- taking sedative or tranquilizers.

When using this product

- avoid alcoholic drinks
- do not drive a motor vehicle or operate machinery, this product will cause drowsiness

Stop use and ask a doctor if:

- sleeplessness persists continuously for more than 2 weeks. Insomnia may be a symptom of serious underlying medical illness.
- pain gets worse or lasts more than 10 days
- fever gets worse or lasts more than 3 days
- redness or swelling is present
- new symptoms occur.

Keep out of reach of children.

If pregnant or breast-feeding, ask a health professional before use.

Directions

- do not exceed recommended dose
- Adults and children 12 years and over:
- take 2 caplets at bedtime.
- do not take more than 2 caplets of this product in 24 hours.
  children under 12 years:
- do not use this adult product in children under 12 years of age; this will provide more than the recommended dose (overdose) and may cause liver damage.

Other Information

- store at 25 °C (77°F) excursions permitted between 15-30°C(59-86°F)
- do not use if imprinted safety seal under cap is broken or missing

this product is not manufactured or distributed by McNeil Consumer Healthcare, owner of the registered trademark Tylenol PM

Inactive Ingredients

Colloidal Silicon Dioxide, Croscarmellose Sodium, FD&C blue #1 aluminum lake, FD&C blue #2 aluminum lake, hypromellose, microcrystalline cellulose, polyethylene glycol, povidone, pregelatinized starch, purified water, Sodium metabisulfite, Sodium starch glycolate, stearic acid, Titanium Dioxide, Talc

Questions or Comments

Call toll free 1-855-314-1850

PACKAGE LABEL.PRINCIPAL DISPLAY PANEL

NDC: 76168-119-25 50 COUNT